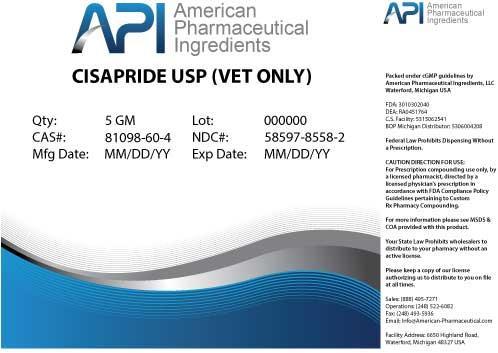 DRUG LABEL: CISAPRIDE
NDC: 58597-8558 | Form: POWDER
Manufacturer: AMERICAN PHARMACEUTICAL INGREDIENTS LLC
Category: other | Type: BULK INGREDIENT
Date: 20140502

ACTIVE INGREDIENTS: CISAPRIDE 1 g/1 g

CISAPRIDE